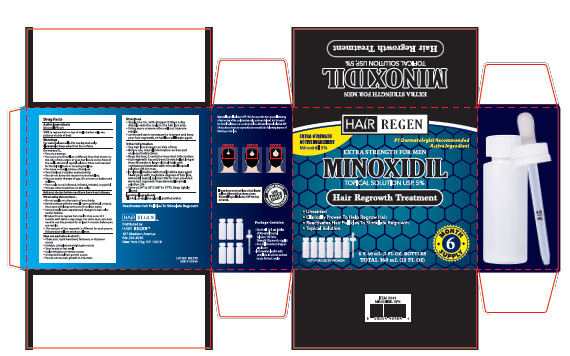 DRUG LABEL: Hair Regen Hair Growth Treatment
NDC: 84232-001 | Form: LIQUID
Manufacturer: YIWU YIZHOU TRADING CO.,LTD
Category: otc | Type: HUMAN OTC DRUG LABEL
Date: 20260104

ACTIVE INGREDIENTS: MINOXIDIL 5 g/100 mL
INACTIVE INGREDIENTS: ALCOHOL 5.6 mL/100 mL; PROPYLENE GLYCOL 61.9 mL/100 mL; WATER 27 mL/100 mL

84232-001

Active Ingredient(s)

Minoxidil 5% w/v

Purpose

Antiseptic, Hand Sanitizer

Use

to regrow hair on top of scalp (vertex only, see pictures on side of box)

Warnings

For external use only. For use by men only.FI ammable: Keep away from fire or flame

Do not use

- You are a woman.
- Your amount of hair loss is different than that shown on the side of this carton or your hair loss is on the front of the scalp. Minoxidil topical solution 5% is not intended for frontal baldness or receding hairline.
- You have no family history of hair loss.
- Your hair loss is sudden and/or patchy.
- You do not know the reason for your hair loss.
- You are under 18 years of age. Do not use on babies and children.
- Your scalp is red, inflamed, infected, rritated, or painful.
- You use other medicines on the scalp.

When using this product.

●Do not apply on other parts of your body.

●Avoid contact with the eyes. In case accidental contact, rinse eyes with large amounts of cool tap water.

●Some people have experienced changes in hair color and/or texture.

●It takes time to regrow hai, results may occur at 2 months with twice a day usage. For some men, you may need to use this product for at least 4 months before you see results.

●The amount of hair regrowth is different for each person. This product will not work on all men,

Stop use

●Chest pain, rapid heartbeat, faintness, or dizziness occurs

●Sudden, unexplained weight gain occurs

●Your hands or feet swell

●Scalp rritation or redness ocurs

●Unwanted facial hair growth occurs

●You do not see hair growth in 4 months

Keep out of reach of children. If swallowed, get medical help or contact a Poison Control Center right away.

Directions

●Apply one mL. with dropper 2 times a day directly onto the scalp in the hair loss area.

●Using more or more often will not improve resufts.

●continued use is necessary to increase and keep your hair regrowth, or hair loss will begin again.

Other information

●See hair loss pictures on side of box

●Before use, read all information on box and enclosed instructions.

●Keep the box, it contains important information.

●Hair regrowth has not been shown to last longer than 48 weeks in large clinical trials with continuous treatment with minoxidil topical sol ution 5% for men.

●In Clinical studies with mostly white men aged 18-49 years with moderate degrees of hair loss, minoxidil topical solution 5% for men provided more hair regrowth than minoxidil topical sol lution 2%

●Store at 20° to 25*C (68° to 77*F). Keep tightly closed